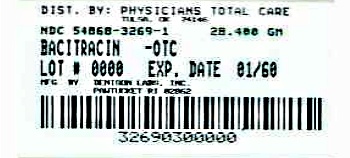 DRUG LABEL: Bacitracin
NDC: 54868-3269 | Form: OINTMENT
Manufacturer: Physicians Total Care, Inc.
Category: otc | Type: HUMAN OTC DRUG LABEL
Date: 20121009

ACTIVE INGREDIENTS: BACITRACIN 500 [USP'U]/1 g
INACTIVE INGREDIENTS: MINERAL OIL; PETROLATUM

Bacitracin

ACTIVE INGREDIENT

Bacitracin 500 units per gram.

PURPOSE

First aid antibiotic.

INDICATIONS

First aid to help prevent infection in minor cuts, scrapes, and burns.

WARNINGS

For external use only. Do not use in the eyes or apply over large areas of the body. In case of deep puncture wounds, animal bites, or serious burns, consult a doctor.

Stop use and consult a doctor

if the condition persists or gets worse, or if a rash or other allergic reaction develops. Do not use if you are allergic to any of the ingredients. Do not use longer than one week unless directed by a doctor.

DIRECTIONS

After gentle washing, apply a small amount (an amount equal to the surface area of the tip of a finger) directly to the affected areas and cover with sterile gauze if desired. May be applied 1 to 3 times daily as the condition indicates.

In case of accidental ingestion, seek professional assistance or contact a Poison Control Center immediately.

Inactive ingredients

ALSO CONTAINS

Mineral oil, white petrolatum

Storage

Store in controlled room temperature 59°-88°F (15°-30°C).

PRINCIPAL DISPLAY PANEL

NDC 54868-3269-1

BACITRACIN OINTMENT U.S.P.

First Aid Antibiotic

NET WT. 1 OZ. (28.35g)

DENISON PHARMACEUTICALS
PAWTUCKET, RI 02862

Additional barcode labeling by:
Physicians Total Care, Inc.
Tulsa, Oklahoma 74146